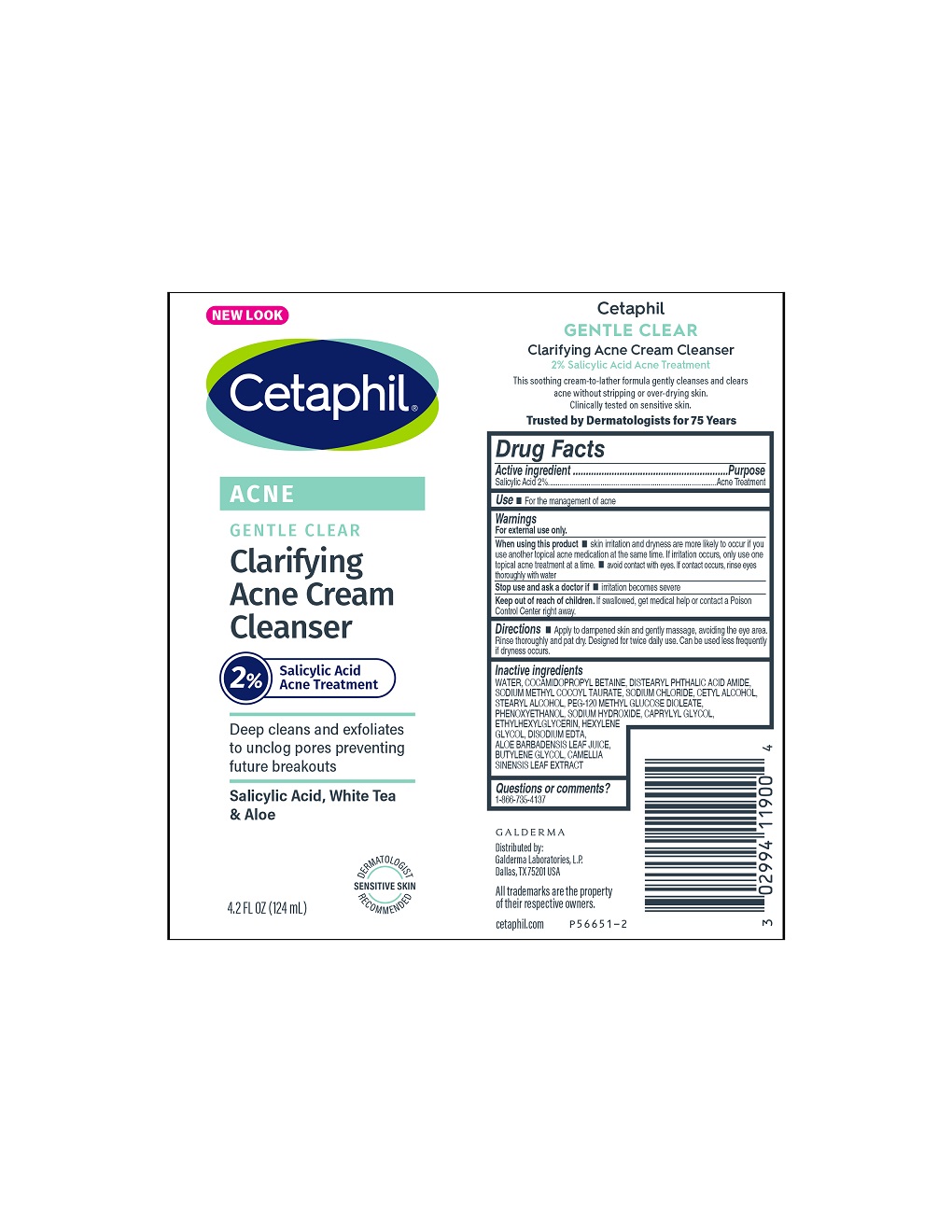 DRUG LABEL: Cetaphil Gentle Clear Clarifying Acne Cleanser
NDC: 0299-4119 | Form: CREAM
Manufacturer: Galderma Laboratories, L.P.
Category: otc | Type: HUMAN OTC DRUG LABEL
Date: 20231120

ACTIVE INGREDIENTS: Salicylic Acid 20 mg/1 mL
INACTIVE INGREDIENTS: Water; Cocamidopropyl Betaine; Distearyl Phthalamic Acid; Sodium Methyl Cocoyl Taurate; Sodium Chloride; Cetyl Alcohol; Stearyl Alcohol; Peg-120 Methyl Glucose Dioleate; Phenoxyethanol; Sodium Hydroxide; Caprylyl Glycol; Ethylhexylglycerin; Hexylene Glycol; Edetate Disodium; Isopropyl Alcohol; Aloe Vera Leaf; Butylene Glycol; Green Tea Leaf

Drug Facts

Active Ingredient

Salicylic Acid 2%

Purpose

Acne Treatment

Use

For the management of acne

Warnings

For external use only

When using this product

- skin irritation and dryness are more likely to occur if you use another topical acne medication at the same time. If irritation occurs, only use one topical acne treatment at a time.
- avoid contact with eyes. If contact occurs, rinse eyes thoroughly with water.

Stop use and ask a doctor if irritation become severe

Keep out of reach of children. If swallowed, get medical help or contact a Poison Control Center right away.

Directions

Apply to dampened skin and gently massage, avoiding the eye area. Rinse thoroughly and pat dry. Designed for twice daily use. Can be used less frequently if dryness occurs.

Inactive Ingredients

Water, Cocamidopropyl Betaine, Distearyl Phthalic Acid Amide, Sodium Methyl Cocoyl Taurate, Sodium Chloride, Cetyl Alcohol, Stearyl Alcohol, PEG-120 Methyl Glucose Dioleate, Phenoxyethanol, Sodium Hydroxide, Caprylyl Glycol, Ethylhexylglycerin, Hexylene Glycol, Disodium EDTA, Isopropyl Alcohol, Aloe Barbadensis Leaf Juice, Butylene Glycol, Camellia Sinensis Leaf Extract

Distributed by:
Galderma Laboratories, L.P.
Dallas, TX 75201 USA
All trademarks are the property
of their respective owners.
cetaphil.com
P56651-2

PRINCIPAL DISPLAY PANEL - 4.2 FL OZ tube

NEW LOOK
Cetaphil

Gentle Clear

Clarifying
Acne Cream
Cleanser

2% Salicylic Acid
Acne Treatment

Deep cleans and exfoliates
to unclog pores preventing
future breakouts

Salicylic Acid, White Tea
& Aloe

Dermatologist Recommended
Sensitive Skin logo
4. 2 FL OZ (124 mL)